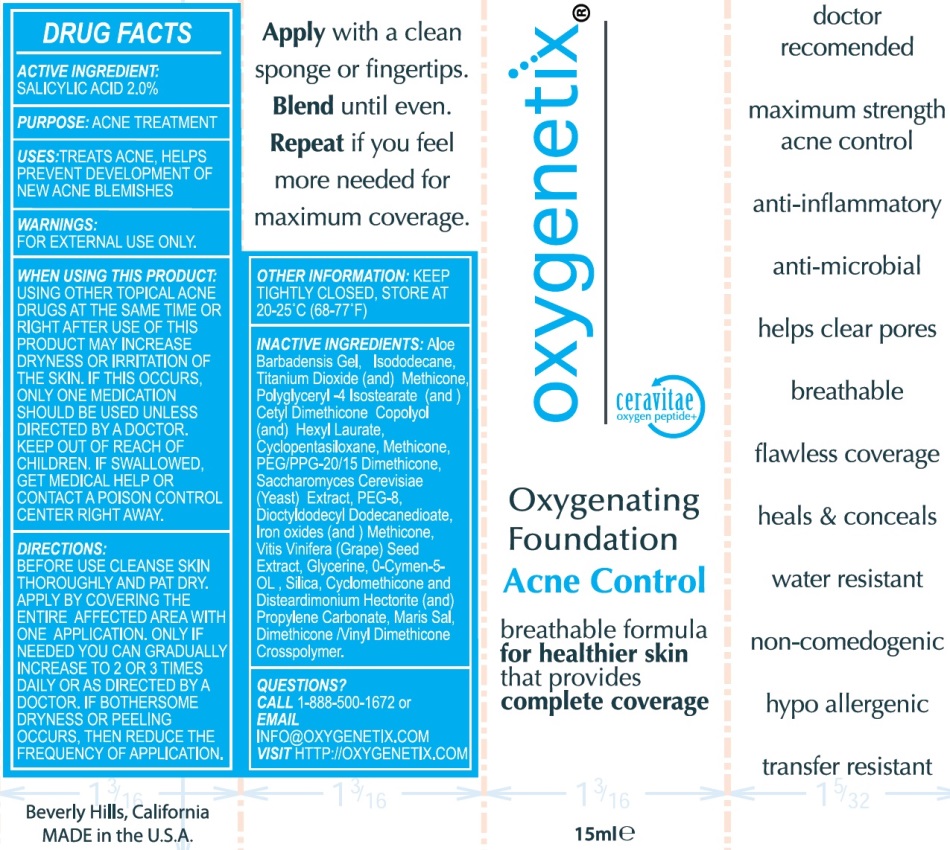 DRUG LABEL: OXYGENETIX OXYGENATING FOUNDATION
NDC: 10258-101 | Form: LOTION
Manufacturer: COLONIAL DAMES CO LTD
Category: otc | Type: HUMAN OTC DRUG LABEL
Date: 20231231

ACTIVE INGREDIENTS: SALICYLIC ACID 2 g/100 mL
INACTIVE INGREDIENTS: ALOE VERA LEAF; ISODODECANE; TITANIUM DIOXIDE; METHICONE (20 CST); POLYGLYCERYL-4 ISOSTEARATE; CETYL DIMETHICONE 150; HEXYL LAURATE; CYCLOMETHICONE 5; PEG/PPG-20/15 DIMETHICONE; SACCHAROMYCES CEREVISIAE; POLYETHYLENE GLYCOL 400; DIOCTYLDODECYL DODECANEDIOATE; FERRIC OXIDE RED; VITIS VINIFERA SEED; GLYCERIN; O-CYMEN-5-OL; SILICON; CYCLOMETHICONE; DISTEARDIMONIUM HECTORITE; PROPYLENE CARBONATE; SEA SALT; DIMETHICONE/VINYL DIMETHICONE CROSSPOLYMER (SOFT PARTICLE)

OXYGENETIX - OXYGENATING FOUNDATION (10258-101)

ACTIVE INGREDIENT:

SALICYLIC ACID 2.0%

PURPOSE:

ACNE TREATMENT

USES:

TREATS ACNE, HELPS PREVENT DEVELOPMENT OF NEW ACNE BLEMISHES

WARNINGS:

FOR EXTERNAL USE ONLY.

WHEN USING THIS PRODUCT:

USING OTHER TOPICAL ACNE DRUGS AT THE SAME TIME OR RIGHT AFTER USE OF THIS PRODUCT MAY INCREASE DRYNESS OR IRRITATION OF THE SKIN. IF THIS OCCURS, ONLY ONE MEDICATION SHOULD BE USED UNLESS DIRECTED BY A DOCTOR.

KEEP OUT OF REACH OF CHILDREN:

IF SWALLOWED, GET MEDICAL HELP OR CONTACT A POISON CONTROL CENTER RIGHT AWAY.

DIRECTIONS:

BEFORE USE CLEANSE SKIN THOROUGHLY AND PAT DRY. APPLY BY COVERING THE ENTIRE AFFECTED AREA WITH ONE APPLICATION. ONLY IF NEEDED YOU CAN GRADUALLY INCREASE TO 2 OR 3 TIMES DAILY OR AS DIRECTED BY A DOCTOR. IF BOTHERSOME DRYNESS OR PEELING OCCURS, THEN REDUCE THE FREQUENCY OF APPLICATION.

OTHER INFORMATION:

KEEP TIGHTLY CLOSED, STORE AT 20-25°C (68-77°F)

INACTIVE INGREDIENTS:

ALOE BARBADENSIS GEL, ISODODECANE, TITANIUM DIOXIDE, METHICONE, POLYGLYCERYL-4 ISOSTEARATE, CETYL DIMETHICONE COPOLYOL, HEXYL LAURATE, CYCLOPENTASILOXANE, PEG/PPG-20/15 DIMETHICONE, SACCHAROMYCES CEREVISIAE, PEG-8, DIOCTYLDODECYL DODECANEDIOATE, IRON OXIDES, VITIS VINIFERA (GRAPE) SEED EXTRACT, GLYCERIN, O-CYMEN-5-OL, SILICA, CYCLOMETHICONE, DISTEARDIMONIUM HECTORITE, PROPYLENE CARBONATE, MARIS SAL, DIMETHICONE/VINYL DIMETHICONE CROSSPOLYMER.

QUESTIONS?

CALL 1-888-500-1672 or EMAIL INFO@OXYGENETIX.COM VISIT HTTP://OXYGENETIX.COM

PACKAGE LABEL

Oxygetix

Oxygenating Foundation Acne Control

15mL